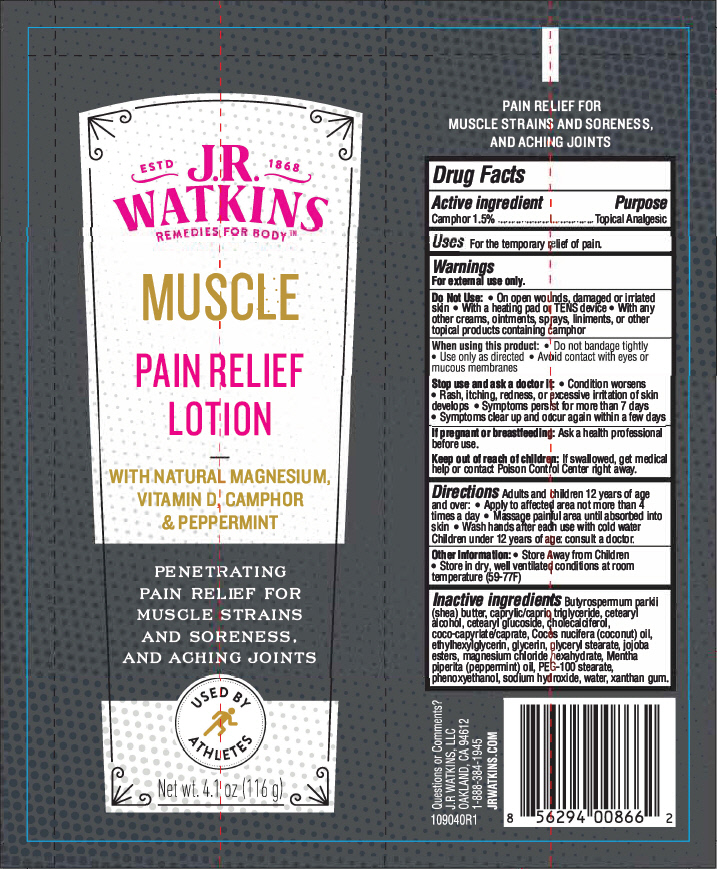 DRUG LABEL: Pain Relief
NDC: 72342-200 | Form: LOTION
Manufacturer: J.R. Watkins, LLC.
Category: otc | Type: HUMAN OTC DRUG LABEL
Date: 20240320

ACTIVE INGREDIENTS: CAMPHOR (NATURAL) 1.5 g/100 g
INACTIVE INGREDIENTS: SHEA BUTTER; MEDIUM-CHAIN TRIGLYCERIDES; CETOSTEARYL ALCOHOL; CETEARYL GLUCOSIDE; CHOLECALCIFEROL; COCOYL CAPRYLOCAPRATE; COCONUT OIL; ETHYLHEXYLGLYCERIN; GLYCERIN; GLYCERYL MONOSTEARATE; HYDROGENATED JOJOBA OIL, RANDOMIZED; MAGNESIUM CHLORIDE; PEPPERMINT OIL; PEG-100 STEARATE; PHENOXYETHANOL; SODIUM HYDROXIDE; WATER; XANTHAN GUM

Pain Relief Lotion
Muscle

Drug Facts

Active ingredient

Camphor 1.5%

Purpose

Topical Analgesic

Uses

For the temporary relief of pain.

Warnings

For external use only.

Do Not Use

- On open wounds, damaged or irriated skin
- With a heating pad or TENS device
- With any other creams, ointments, sprays, liniments, or other topical products containing camphor

When using this product

- Do not bandage tightly
- Use only as directed
- Avoid contact with eyes or mucous membranes

Stop use and ask a doctor if

- Condition worsens
- Rash, itching, redness, or excessive irritation of skin develops
- Symptoms persist for more than 7 days
- Symptoms clear up and occur again within a few days

If pregnant or breastfeeding

Ask a health professional before use.

Keep out of reach of children

If swallowed, get medical help or contact Poison Control Center right away.

Directions

Adults and children 12 years of age and over:

- Apply to affected area not more than 4 times a day
- Massage painful area until absorbed into skin
- Wash hands after each use with cold water

Children under 12 years of age: consult a doctor.

Other Information

- Store Away from Children
- Store in dry, well ventilated conditions at room temperature (59-77F)

Inactive ingredients

Butyrospermum parkii (shea) butter, caprylic/capric triglyceride, cetearyl alcohol, cetearyl glucoside, cholecalciferol, coco-capyrlate/caprate, Cocos nucifera (coconut) oil, ethylhexylglycerin, glycerin, glyceryl stearate, jojoba esters, magnesium chloride hexahydrate, Mentha piperita (peppermint) oil, PEG-100 stearate, phenoxyethanol, sodium hydroxide, water, xanthan gum.

Questions or Comments?

J.R WATKINS, LLC
OAKLAND, CA 94612
1-888-384-1945

PRINCIPAL DISPLAY PANEL - 116 g Tube Label

ESTD
1868

J.R
WATKINS
REMEDIES FOR BODY™

MUSCLE

PAIN RELIEF
LOTION

WITH NATURAL MAGNESIUM,
VITAMIN D, CAMPHOR
& PEPPERMINT

PENETRATING
PAIN RELIEF FOR
MUSCLE STRAINS
AND SORENESS,
AND ACHING JOINTS

USED BY
ATHLETES

Net wt. 4.1 oz (116 g)